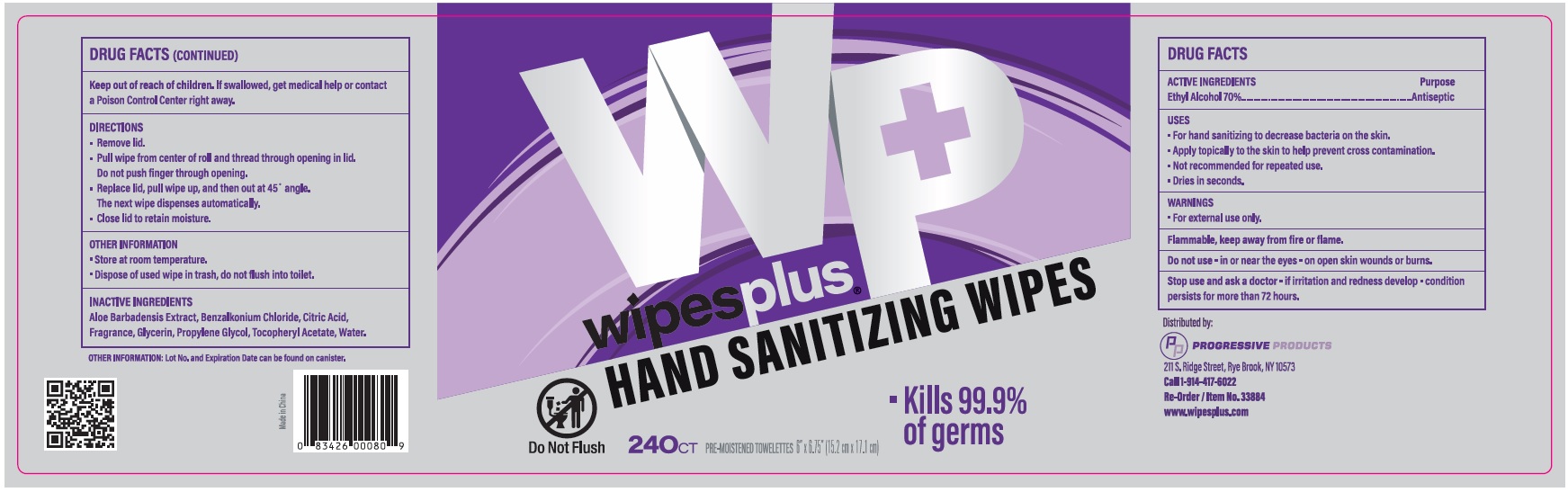 DRUG LABEL: Wipesplus Hand Sanitizing Wipes
NDC: 67151-737 | Form: CLOTH
Manufacturer: Progressive Products, LLC
Category: otc | Type: HUMAN OTC DRUG LABEL
Date: 20221014

ACTIVE INGREDIENTS: ALCOHOL 0.7 mL/1 1
INACTIVE INGREDIENTS: CITRIC ACID MONOHYDRATE; WATER; .ALPHA.-TOCOPHEROL ACETATE; PROPYLENE GLYCOL; GLYCERIN; ALOE VERA LEAF; BENZALKONIUM CHLORIDE

Drug Facts

Active Ingredient

Ethyl Alcohol 70%

Purpose

Antiseptic

Uses

- For hand sanitizing to decrease bacteria on the skin.
- Apply topically to the skin to help prevent cross contamination
- Not recommended for repeated use.
- Dries in seconds.

Warnings

For external use only.

Flammable, keep away from fire or flame.

Do not use

- in or near the eyes
- on open skin wounds or burns.

Stop use and ask a doctor

- if irritation and redness develop
- condition persists for more than 72 hours.

Keep out of reach of children

If swallowed, get medical help or contact a Poison Control Center right away.

Directions

- Remove lid.
- Pull wipe from center of roll and thread theough opening in lid. Do not push finger through opening.
- Replace lid, pull wipe up, and then at 45° angle. The next wipe dispenses automatically.
- Close lid to retain moisture.

Other Information

- Store at room temperature.
- Dispose of used wipe in trash, do not flush into toilet.

Inactive Ingredients

Aloe Barbadensis Extract, Benzalkonium Chloride, Citric Acid, Fragrance, Glycerin, Propylene Glycol, Tocopheryl Acetate, Water

Principal Display Panel

wipesplus

HAND SANITIZING WIPES

- Killes 99.9% of germs

240 CT